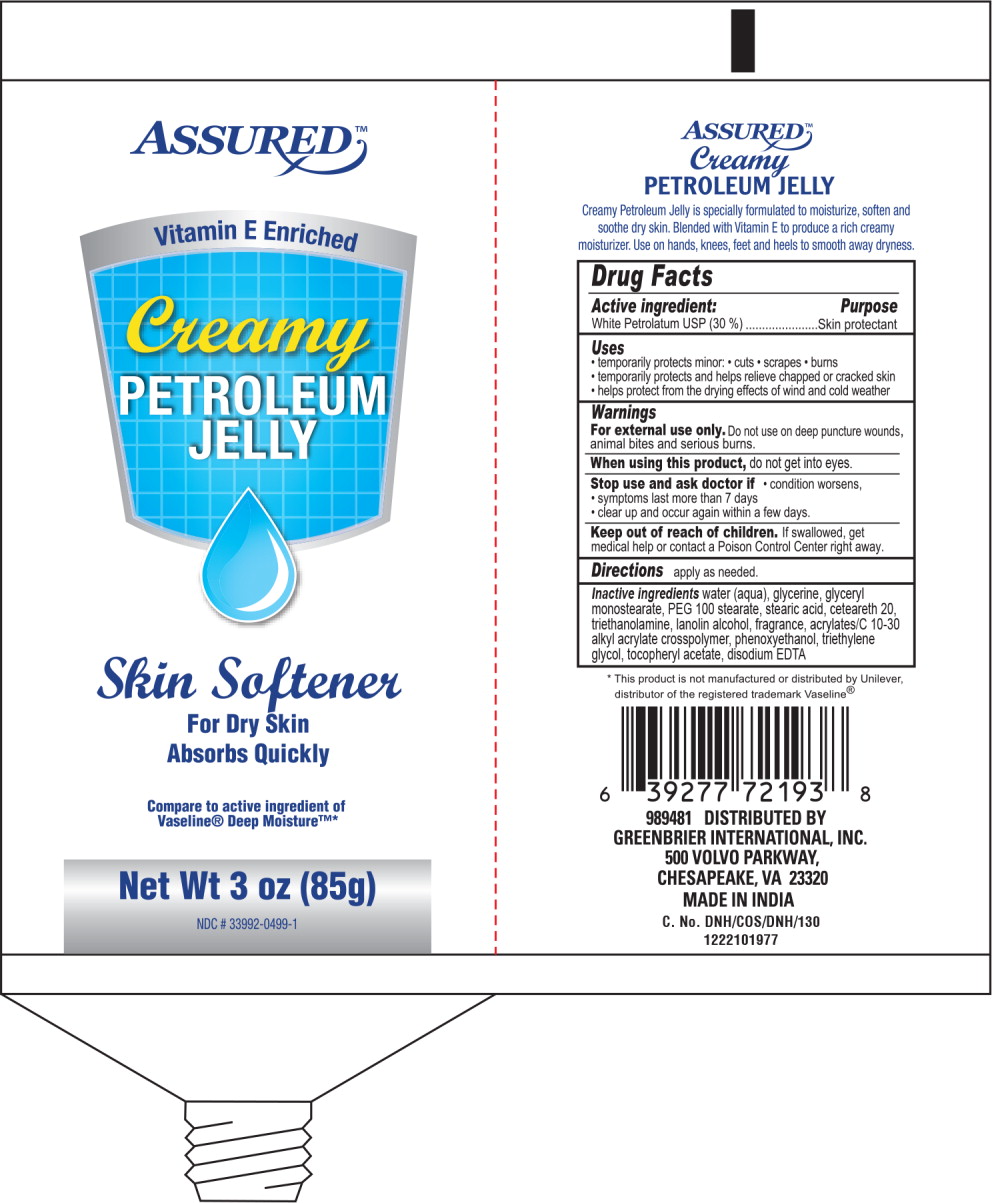 DRUG LABEL: Petrolatum
NDC: 33992-0499 | Form: CREAM
Manufacturer: Greenbrier International, Inc.
Category: otc | Type: HUMAN OTC DRUG LABEL
Date: 20190204

ACTIVE INGREDIENTS: Petrolatum 30 g/100 g
INACTIVE INGREDIENTS: Water; GLYCERIN; GLYCERYL MONOSTEARATE; PEG-100 STEARATE; STEARIC ACID; POLYOXYL 20 CETOSTEARYL ETHER; TROLAMINE; LANOLIN ALCOHOLS; CARBOMER COPOLYMER TYPE A (ALLYL PENTAERYTHRITOL CROSSLINKED); PHENOXYETHANOL; TRIETHYLENE GLYCOL; .ALPHA.-TOCOPHEROL ACETATE; EDETATE DISODIUM

Drug Facts

Active ingredient:

White Petrolatum USP (30 %)

Purpose

Skin protectant

Uses

- temporarily protects minor:
  - cuts
  - scrapes
  - burns
- temporarily protects and helps relieve chapped or cracked skin
- helps protect from the drying effects of wind and cold weather

Warnings

For external use only.

Do not use on deep puncture wounds, animal bites and serious burns.

When using this product, do not get into eyes.

Stop use and ask doctor if

- condition worsens,
- symptoms last more than 7 days
- clear up and occur again within a few days.

Keep out of reach of children.

If swallowed, get medical help or contact a Poison Control Center right away.

Directions

Apply as needed.

Inactive ingredients

water (aqua), glycerine, glyceryl monostearate, PEG 100 stearate, stearic acid, ceteareth 20, triethanolamine, lanolin alcohol, fragrance, acrylates/C 10-30 alkyl acrylate crosspolymer, phenoxyethanol, triethylene glycol, tocopheryl acetate, disodium EDTA

Principal Display Panel - Petroleum Jelly Tube Label

ASSURED™

Vitamin E Enriched

Creamy
PETROLEUM
JELLY

Skin Softener

For Dry Skin

Absorbs Quickly

Compare to active ingredient of
Vaseline® Deep Moisture™

Net Wt 3 oz (85g)

NDC # 33992-0499-1